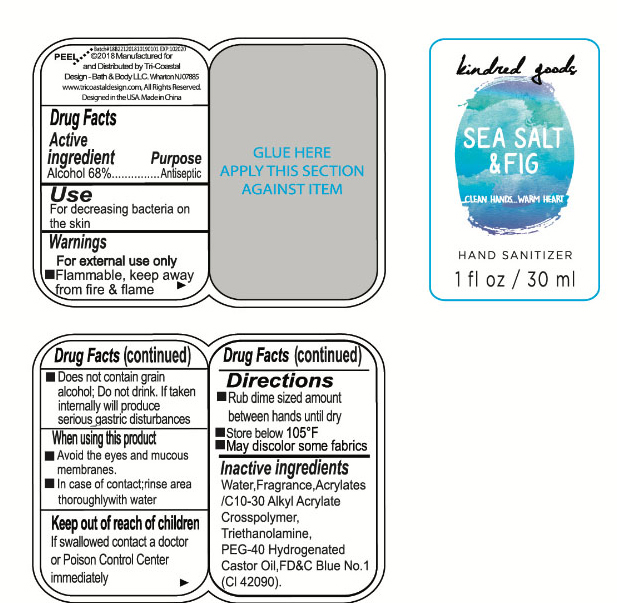 DRUG LABEL: kindred goods
NDC: 49852-403 | Form: LIQUID
Manufacturer: Tri-Coastal Design Company Inc.
Category: otc | Type: HUMAN OTC DRUG LABEL
Date: 20180924

ACTIVE INGREDIENTS: ALCOHOL 68 g/100 mL
INACTIVE INGREDIENTS: FD&C BLUE NO. 1; TROLAMINE; POLYOXYL 40 HYDROGENATED CASTOR OIL; WATER; CARBOMER COPOLYMER TYPE A (ALLYL PENTAERYTHRITOL CROSSLINKED)

Drug Facts

Active ingredient

Alcohol 68%

Purpose

Antiseptic

Use

For decreasing bacteria on the skin

Warnings

For external use only ■ Flammable, keep away from fire & flame ■ Does not contain grain alcohol;Do not drink. If taken internally will produce serious gastric disturbances

When using this product

■ Avoid the eyes and mucous membranes ■ In the case of contact, rinse area thoroughly with water

Keep out of reach of children

If swallowed contact a doctor or Poison Control Center immediately.

Directions

■ Rub dime sized amount between hands until dry ■ Store below 105ºF ■ May discolor some fabrics

Inactive ingredients

Water, Fragrance, Acrylates/C10-30 Alkyl Acrylate Crosspolymer, Triethanolamine, PEG-40 Hydrogenated Castor Oil, FD&C Blue No. 1 (CI 42090)